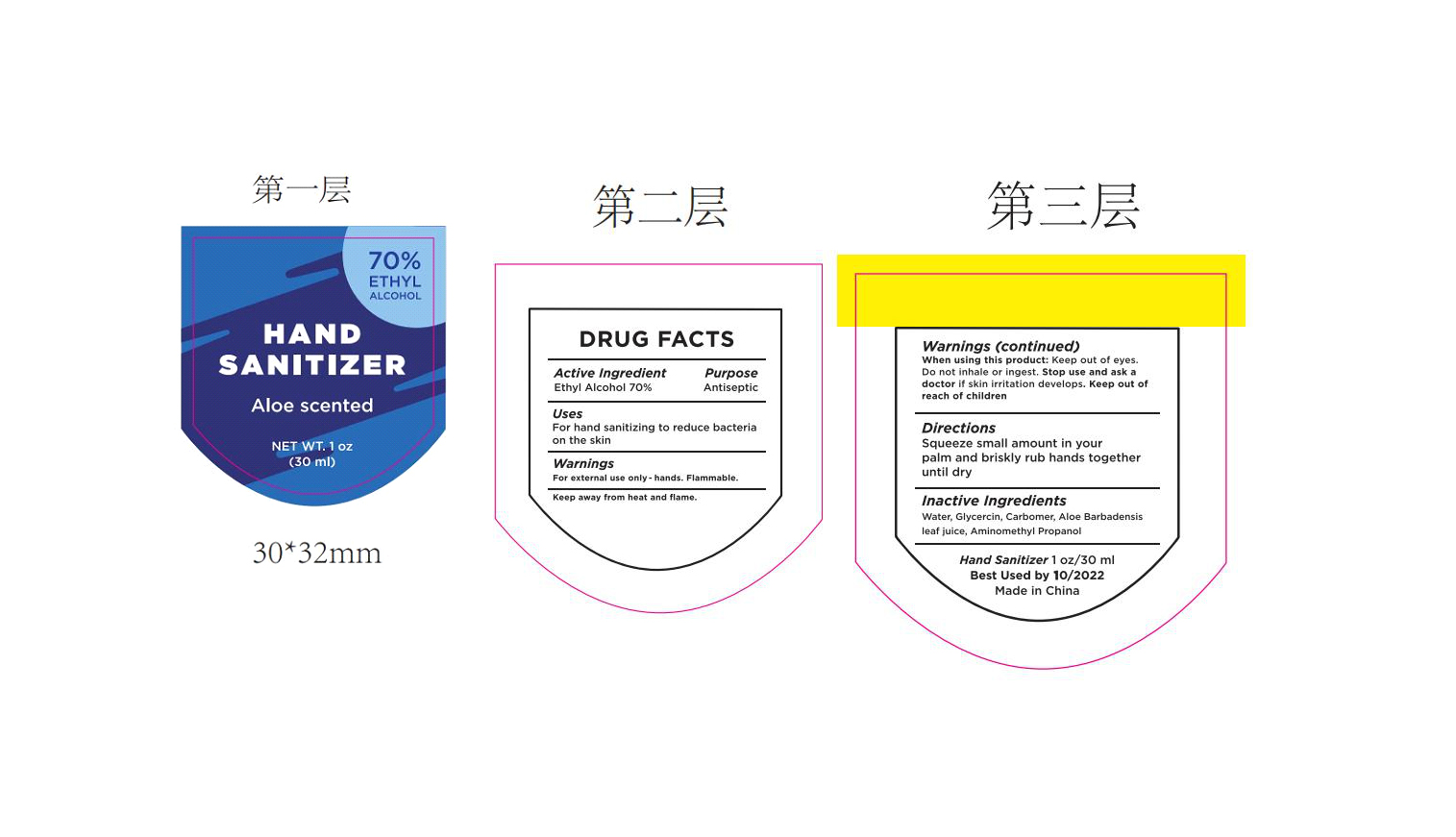 DRUG LABEL: HAND SANITIZER
NDC: 47993-321 | Form: GEL
Manufacturer: NINGBO JIANGBEI OCEAN STAR TRADING CO.,LTD
Category: otc | Type: HUMAN OTC DRUG LABEL
Date: 20201125

ACTIVE INGREDIENTS: ALCOHOL 70 g/112 mL
INACTIVE INGREDIENTS: WATER; GLYCERIN; CARBOMER 940; ALOE VERA LEAF; AMINOMETHYLPROPANOL

47993-321

Active Ingredients

Ethyl alcohol 70%

PURPOSE

Antiseptic

Uses：

For hand sanitizing to reduce bacteria on the skin.

Warnings:

For external use only-hands.Flammable.Keep away from heat and flame.

when using this product: Keep out of eyes. Do not inhale or ingest.

Stop use and ask a doctor if Skin irritation develops.

Keep out of reach of children.

Directions:

Squeeze small amount in your palm and briskly rub hands together until dry.

Inactive Ingredients:

Water, Glycerin, Carbomer, Aloe Barbadensis leaf juice, Aminomethyl Propanol.